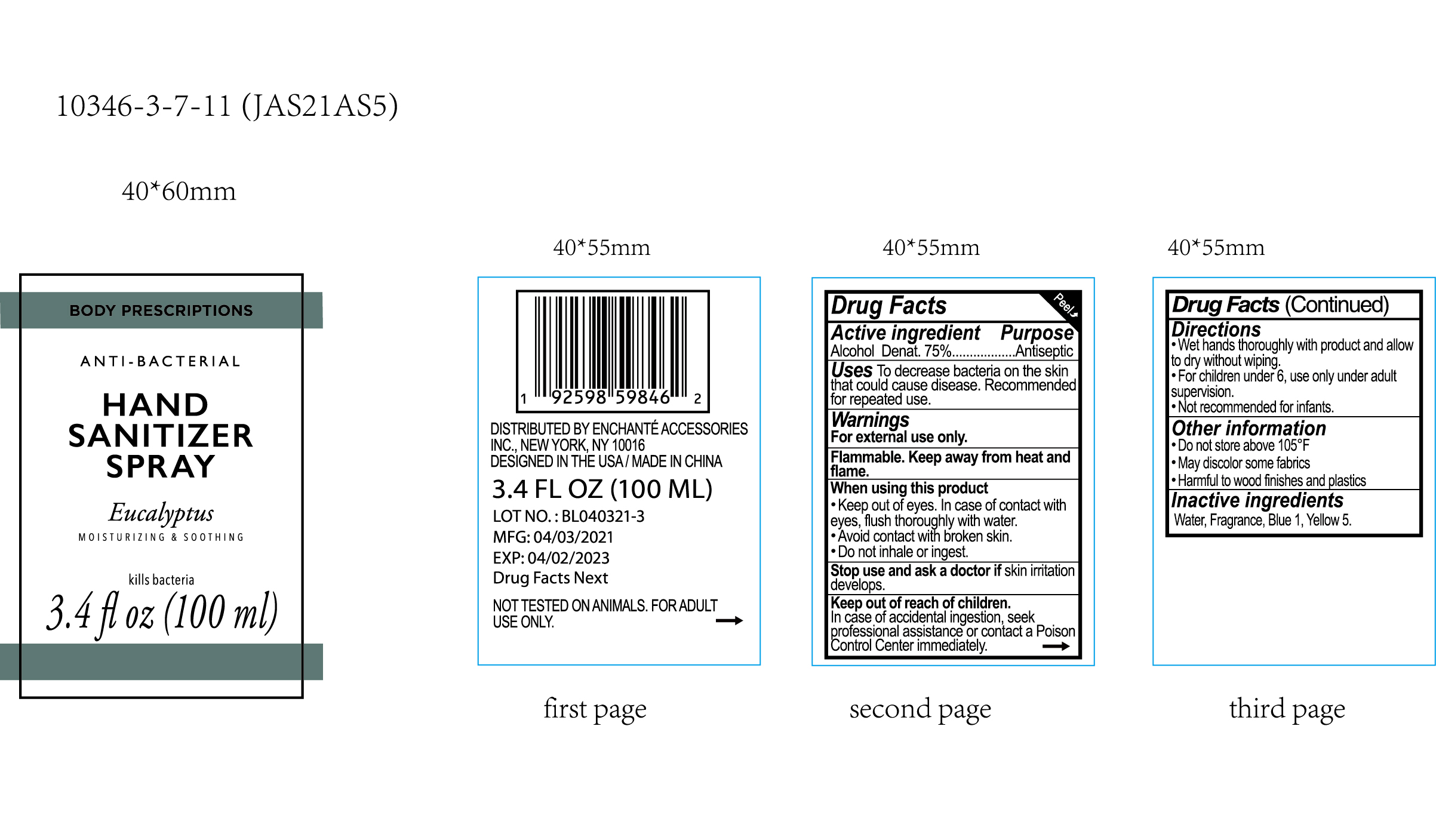 DRUG LABEL: BODY PRESCRIPTIONS Eucalyptus ANTIBACTERIAL HAND SANITIZER
NDC: 50563-418 | Form: SPRAY
Manufacturer: ENCHANTE ACCESSORIES INC.
Category: otc | Type: HUMAN OTC DRUG LABEL
Date: 20210326

ACTIVE INGREDIENTS: ALCOHOL 75 mL/100 mL
INACTIVE INGREDIENTS: WATER; FD&C YELLOW NO. 5; FD&C BLUE NO. 1

50563-418/JAS21AS5

Active Ingredient

Alcohol Denat: 75%

Purpose

Antiseptic

Use

■ To decrease bacteria on the skin that could cause disease
■Recommended for repeated use

WARNINGS

For external use only

Flammable. Keep away from heat and flame

When using this product

keep out of eyes. In case of contact with eyes, flush thoroughly with water

Avoid contact with broken skin

Do not inhale or ingest

Stop use and ask a doctor if skin irritation develops

Keep out of reach of children. In case of accidental ingestion, seek professional assistance or contact a Poison Control Center immediately

Directions

Wet hands thoroughly with product and allow to dry without wiping

For children under 6, use only under adult supervision

Not recommended for infants

Other information

Do not store above 105F

May discolor some fabrics

Harmful to wood finishes and plastics

Inactive ingredients

Water, Fragrance, Blue 1, Yellow 5